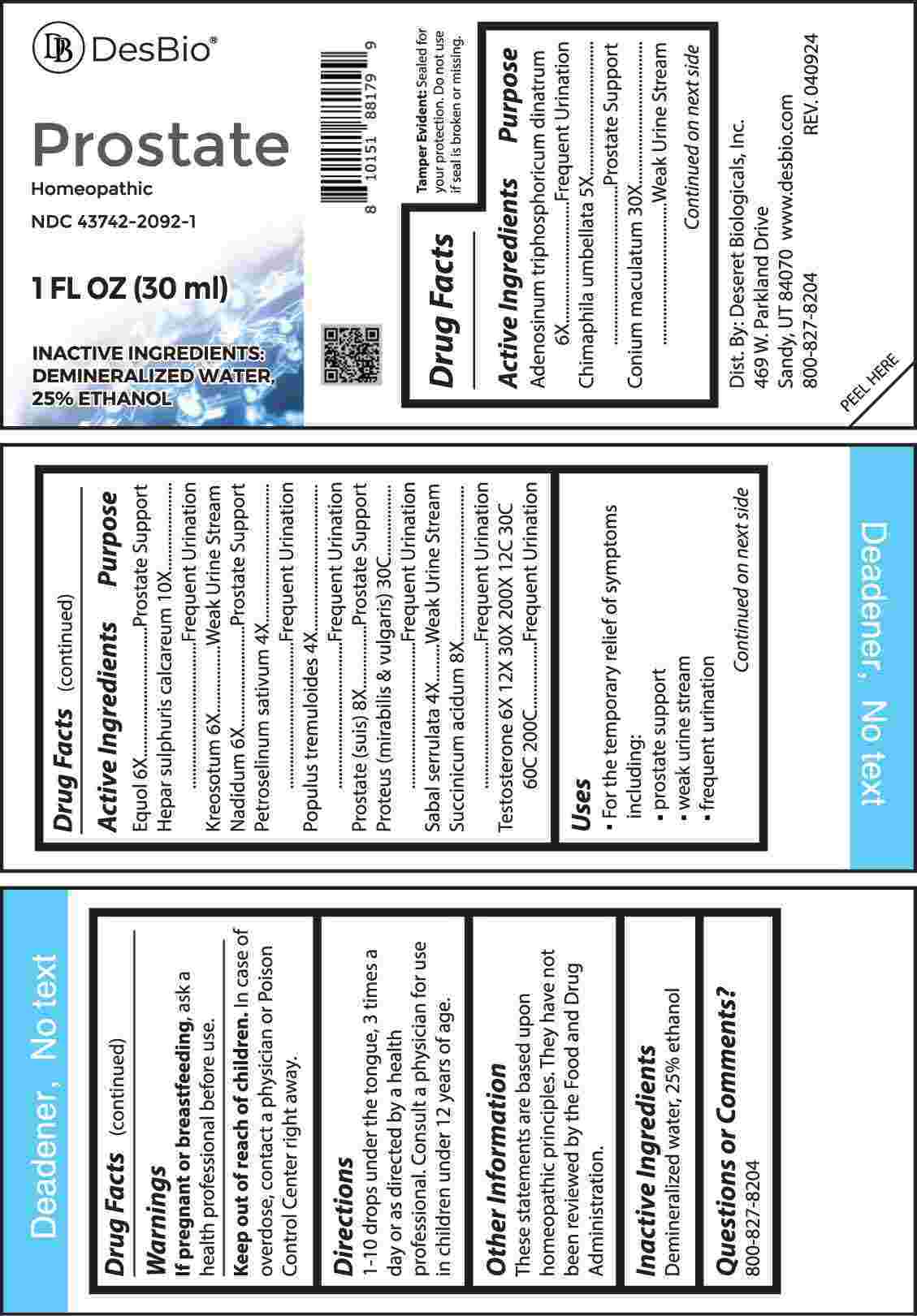 DRUG LABEL: Prostate
NDC: 43742-2092 | Form: LIQUID
Manufacturer: Deseret Biologicals, Inc.
Category: homeopathic | Type: HUMAN OTC DRUG LABEL
Date: 20240819
DEA Schedule: CIII

ACTIVE INGREDIENTS: PETROSELINUM CRISPUM WHOLE 4 [hp_X]/1 mL; POPULUS TREMULOIDES BARK 4 [hp_X]/1 mL; POPULUS TREMULOIDES LEAF 4 [hp_X]/1 mL; SAW PALMETTO 4 [hp_X]/1 mL; CHIMAPHILA UMBELLATA WHOLE 5 [hp_X]/1 mL; ADENOSINE TRIPHOSPHATE DISODIUM 6 [hp_X]/1 mL; EQUOL 6 [hp_X]/1 mL; WOOD CREOSOTE 6 [hp_X]/1 mL; NADIDE 6 [hp_X]/1 mL; TESTOSTERONE 6 [hp_X]/1 mL; SUS SCROFA PROSTATE 8 [hp_X]/1 mL; SUCCINIC ACID 8 [hp_X]/1 mL; CALCIUM SULFIDE 10 [hp_X]/1 mL; CONIUM MACULATUM FLOWERING TOP 30 [hp_X]/1 mL; PROTEUS MIRABILIS 30 [hp_C]/1 mL; PROTEUS VULGARIS 30 [hp_C]/1 mL
INACTIVE INGREDIENTS: WATER; ALCOHOL

DRUG FACTS:

ACTIVE INGREDIENTS:

Adenosinum Triphosphoricum Dinatrum 6X, Chimaphila Umbellata 5X, Conium Maculatum 30X, Equol 6X, Hepar Sulphuris Calcareum 10X, Kreosotum 6X, Nadidum 6X, Petroselinum Sativum 4X, Populus Tremuloides 4X, Prostate (Suis) 8X, Proteus (Mirabilis) 30C, Proteus (Vulgaris) 30C, Sabal Serrulata 4X, Succinicum Acidum 8X, Testosterone 6X, 12X, 30X, 200X, 12C, 30C, 60C, 200C.

PURPOSE:

Adenosinum Triphosphoricum Dinatrum – Frequent Urination, Chimaphila Umbellata – Prostate Support, Conium Maculatum – Weak Urine Stream, Equol – Prostate Support, Hepar Sulphuris Calcareum – Frequent Urination, Kreosotum – Weak Urine Stream, Nadidum – Prostate Support, Petroselinum Sativum – Frequent Urination, Populus Tremuloides – Frequent Urination, Prostate (Suis) – Prostate Support, Proteus (Mirabilis) – Frequent Urination, Proteus (Vulgaris) – Frequent Urination, Sabal Serrulata – Weak Urine Streak, Succinicum Acidum – Frequent Urination, Testosterone – Frequent Urination

USES:

• For the temporary relief of the symptoms including:

• prostate support • weak urine stream • frequent urination

These statements are based upon homeopathic principles. They have not been reviewed by the Food and Drug Administration.

WARNINGS:

If pregnant or breast-feeding, ask a health professional before use.

Keep out of reach of children. In case of overdose, contact a physician or Poison Control Center right away.

Tamper Evident: Sealed for your protection. Do not use if seal is broken or missing.

KEEP OUT OF REACH OF CHILDREN:

In case of overdose, contact a physician or Poison Control Center right away.

DIRECTIONS:

1-10 drops under the tongue, 3 times a day or as directed by a health professional. Consult a physician for use in children under 12 years of age.

INACTIVE INGREDIENTS:

Demineralized water, 25% ethanol

QUESTIONS:

Dist. By: Deseret Biologicals, Inc.

469 W. Parkland Drive

Sandy, UT 84070

www.desbio.com

800-827-8204

PACKAGE LABEL DISPLAY:

Des Bio

Prostate

Homeopathic

NDC 43742-2092-1

1 FL OZ (30 ml)